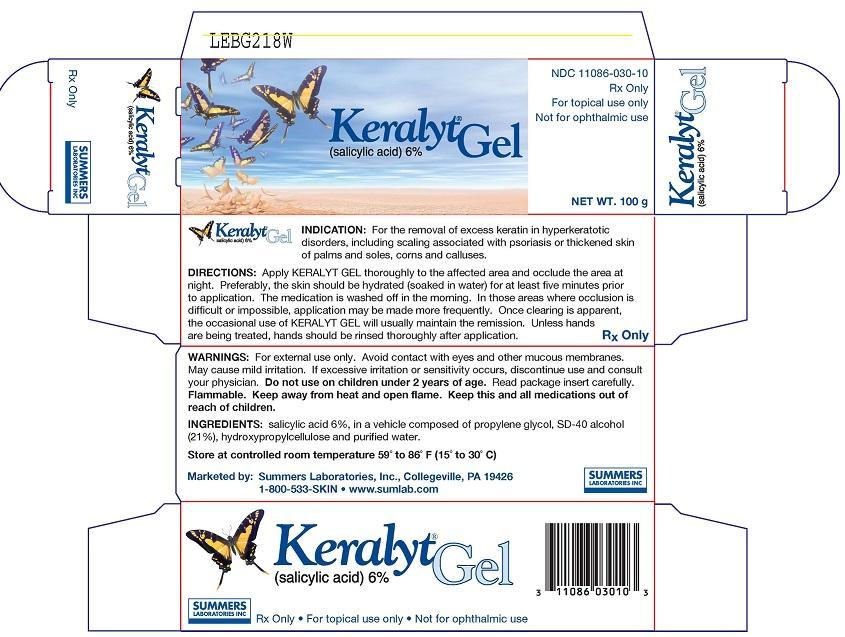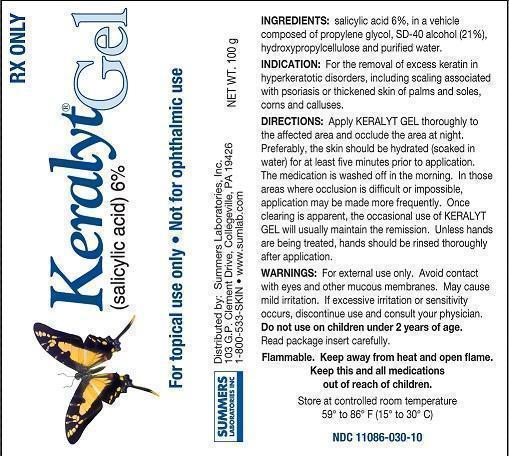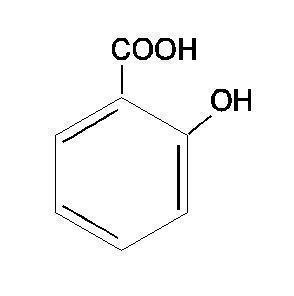 DRUG LABEL: Keralyt
NDC: 11086-030 | Form: GEL
Manufacturer: Summers Laboratories Inc
Category: prescription | Type: HUMAN PRESCRIPTION DRUG LABEL
Date: 20240327

ACTIVE INGREDIENTS: SALICYLIC ACID 6 g/100 g
INACTIVE INGREDIENTS: PROPYLENE GLYCOL; ALCOHOL; HYDROXYPROPYL CELLULOSE; WATER

Summers Laboratories (as PLD) - Keralyt Gel (Salicylic Acid) 6% (11086-030)

DESCRIPTION

DESCRIPTION:KERALYT® is a gel for topical administration containing salicylic acid 6%, in a vehicle composed of propylene glycol, SD-40 alcohol (21%), hydroxypropylcellulose and purified water. Salicylic acid is the 2 hydroxy derivative of benzoic acid having the following structure:

CLINICAL PHARMACOLOGY

CLINICAL PHARMACOLOGY:Salicylic acid has been shown to produce desquamation of the horny layer of skin while not affecting qualitative or quantitative changes in structure of the viable epidermis. ¹, ²The mechanism of action has been attributed to a dissolution of intercellular cement substance. ³In a study of the percutaneous absorption of salicylic acid from KERALYT GEL in four patients with extensive active psoriasis, Taylor and Halprin ⁴showed that peak serum salicylate levels never exceeded 5 mg/100 ml even though more than 60% of the applied salicylic acid was absorbed. Systemic toxic reactions are usually associated with much higher serum levels (30 to 40 mg/100 ml). Peak serum levels occurred within 5 hours of the topical application under occlusion. The sites were occluded for 10 hours over the entire body surface below the neck. Since salicylates are distributed in the extracellular space, patients with a contracted extracellular space due to dehydration or diuretics have higher salicylate levels than those with a normal extracellular space. ⁵(See PRECAUTIONS).

The major metabolites identified in the urine after topical administration are salicyluric acid (52%), salicylate glucuronides (42%), and free salicylic acid (6%). ³The urinary metabolites after percutaneous absorption differ from those after oral salicylate administration; those derived from percutaneous absorption contain more glucuronides and less salicyluric and salicylic acid. Almost 95% of a single dose of salicylate is excreted within 24 hours of its entrance into the extracellular space. ⁵

Fifty to eighty percent of salicylate is protein bound to albumin. Salicylates compete with the binding of several drugs and can modify the action of these drugs. By similar competitive mechanisms other drugs can influence the serum levels of salicylate. ⁵(See PRECAUTIONS).

INDICATIONS AND USAGE- For the removal of excess keratin in hyperkeratotic disorders, including scaling associated with scalp psoriasis or thickened skin of palms and soles, corns and calluses.

CONTRAINDICATIONS

CONTRAINDICATIONS:KERALYT GEL should not be used in any patient known to be sensitive to salicylic acid or any other listed ingredient. KERALYT should not be used in children under 2 years of age.

WARNINGS

WARNINGS:Prolonged use over large areas, especially in children and those patients with significant renal or hepatic impairment, could result in salicylism. Concomitant use of other drugs which may contribute to elevated serum salicylate levels should be avoided where the potential for toxicity is present. In children under 12 years of age and those patients with renal or hepatic impairment, the area to be treated should be limited and the patient monitored closely for signs of salicylate toxicity: nausea, vomiting, dizziness, loss of hearing, tinnitus, lethargy, hyperpnoea, diarrhea, psychic disturbances. In the event of salicylic acid toxicity, the use of KERALYT GEL should be discontinued. Fluids should be administered to promote urinary excretion. Treatment with sodium bicarbonate (oral or intravenous) should be instituted as appropriate.

Considering the potential risk of developing Reye’s Syndrome, salicylate products should not be administered to children or teenagers with varicella or influenza, unless directed by a physician.

PRECAUTIONS

PRECAUTIONS:For external use only. Avoid contact with eyes and other mucous membranes. Mild burning or stinging may occur. Peeling of the skin may increase as the salicylic acid works to loosen excess keratin. If excessive burning, stinging or peeling occurs, discontinue use and consult your physician. Flammable. Keep away from heat and open flame. Keep this and all medications out of reach of children.

DRUG INTERACTIONS

Drug Interactions.(The following interactions are from a published review ⁵and include reports concerning both oral and topical salicylate administration. The relationship of these interactions to the use of KERALYT GEL is not known.)

I. Due to the competition of salicylate with other drugs for binding to serum albumin the following drug interactions may occur:

Drug | Description of Interaction
Tolbutamide; Sulfonylureas | Hypoglycemia potentiated
Methotrexate | Decreases tubular reabsorption; clinical toxicity from methotrexate can result
Oral Anticoagulant | Increased bleeding

II. Drugs changing salicylate levels by altering renal tubular reabsorption:

Drug | Description
Corticosteroids | Decreases plasma salicylate level; Tapering doses of steroids may promote salicylism
Ammonium Sulfate | Increases plasma salicylate level

III. Drugs with complicated interactions with salicylates:

Drug | Description
Heparin | Salicylate decreases platelet adhesiveness and interferes with hemostasis in heparin-treated patients
Pyrazinamide | Inhibits pyrazinamide-induced hyperuricemia
Uricosuric Agents | Effect of probenecid, sulfinpyrazone and phenylbutazone inhibited

The following alterations of laboratory tests have been reported during salicylate therapy ⁶:

Laboratory Tests | Effect of Salicylates
Thyroid Function | Decreased PBI; increased T3uptake
Urinary Sugar | False negative with glucose oxidase; false positive with Clinitest with high-dose salicylate therapy (2-5 g qd)
5 Hydroxyindole acetic acid | False negative with fluorometric test
Acetone, Ketone Bodies | False positive FeCl3in Gerhardt reaction; red color persists with boiling
17-OH corticosteroids | False reduced values with >4.8 g qd salicylate
Vanilmandelic Acid | False reduced values
Uric Acid | May increase or decrease depending on dose
Prothrombin | Decreased levels; slightly increased prothrombin time

PREGNANCY

Pregnancy (Category C):Salicylic acid has been shown to be teratogenic in rats and monkeys. It is difficult to extrapolate from oral doses of acetyl salicylic acid used in these studies to topical administration as the oral dose to monkeys may represent 4 times the maximum daily human dose of salicylic acid (as supplied in one tube, 40 g of KERALYT GEL) when applied topically over a large body surface. There are no adequate and well-controlled studies in pregnant women. KERALYT GEL should be used during pregnancy only if the potential benefit justifies the risk to the fetus.

NURSING MOTHERS

Nursing Mothers:Because of the potential for serious adverse reactions in nursing infants from the mother’s use of KERALYT GEL, a decision should be made whether to discontinue nursing or to discontinue the drug, taking into account the importance of the drug to the mother.

CARCINOGENESIS AND MUTAGENESIS AND IMPAIRMENT OF FERTILITY

Carcinogenesis, Mutagenesis, Impairment of Fertility:No data are available concerning potential carcinogenic or reproductive effects of KERALYT GEL. It has been shown to lack mutagenic potential in the Ames Salmonella test.

ADVERSE REACTIONS

ADVERSE REACTIONS:Excessive erythema and scaling conceivably could result from use on open skin lesions.

OVERDOSAGE- See WARNINGS

DOSAGE AND ADMINISTRATION- The preferable method of use is to apply KERALYT GEL thoroughly to the affected area and occlude the area at night. Preferably, the skin should be hydrated for at least five minutes prior to application. The medication is washed off in the morning and if excessive drying and/or irritation is observed a bland cream or lotion may be applied. Once clearing is apparent, the occasional use of KERALYT GEL will usually maintain the remission. In those areas where occlusion is difficult or impossible, application may be made more frequently; hydration by wet packs or baths prior to application apparently enhances the effect. Unless hands are being treated, hands should be rinsed thoroughly after application. For use as a scalp treatment:KERALYT GEL should be applied directly to the affected areas of the scalp on a frequency directed by your physician. The applicator tip will provide accurate application, avoiding contact with normal hair or skin. The gel should be washed off after 10 to 20 minutes initially, but it can be left on for up to an hour as treatment progresses. The gel can be washed off using KERALYT SHAMPOO or warm water in a bath or shower.

REFERENCES:

1. Davies M, Marks R: Br J Dermatol95: 187-192,1976.
2. Marks R, Davies M, Cattel A: J Invest Dermatol64: 283, 1975.
3. Huber C, Christophers E: Arch Derm Res257: 293-297, 1977.
4. Taylor JR, Halprin KM: Arch Dermatol111: 740-743, 1975.
5. Goldsmith LA: Int J Dermatol18: 32-36.
6. Wilson JG, Ritter EJ, Scott WJ, Fradlein R: Tox Appl Pharmacol41: 67-78, 1977.

SUMMERS
LABORATORIES INC

Manufactured by:
EMS Contract Packaging, Hatfield, PA 19440
Distributed by:
Summers Laboratories, Inc. Collegeville, PA 19426
1-800-533-SKIN (7546) • www.sumlab.com
KERALYT is a trademark of Summers Laboratories, Inc.